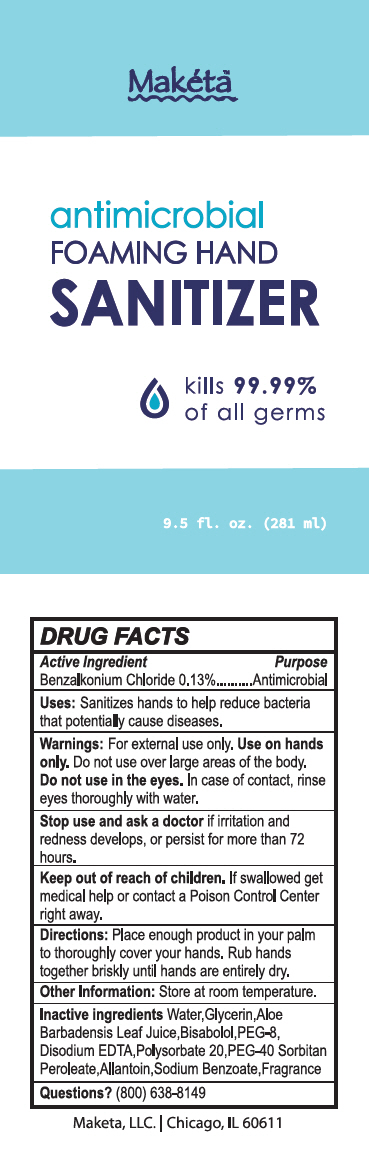 DRUG LABEL: Antibacterial Foaming Hand Sanitizer
NDC: 72102-056 | Form: LIQUID
Manufacturer: Maketa,LLC
Category: otc | Type: HUMAN OTC DRUG LABEL
Date: 20200407

ACTIVE INGREDIENTS: Benzalkonium Chloride 1.3 mg/1 mL
INACTIVE INGREDIENTS: water; .ALPHA.-BISABOLOL, (+/-)-; Allantoin; Aloe vera leaf; Edetate Disodium Anhydrous; PEG-8 Stearate; PEG-40 Sorbitan diisostearate; Glycerin; Sodium Benzoate; Polysorbate 20

Antibacterial Foaming Hand Sanitizer

Drug Facts

Active Ingredients

Benzalkonium Chloride

Purpose

Antimicrobial

Uses

Sanitizes hands to help reduce bacteria that potentially cause diseases.

Warnings

For External use only. Use on hands only. Do not use over large areas of the body.

Do not use in the eyes. In case of contact, rinse eyes thoroughly with water.

Stop Use and ask a doctor if irritation and redness develops , or persist for more than 72 hours.

Keep out of reach of children

If swallowed, get medical help or contact a Poison Control Center right away.

Directions

Place enough product in your palm to thoroughly cover your hands. Rub hands together briskly until hands are entirely dry.

Other information

Store at room temperature.

Inactive Ingredients

Leaf Juice, Water, Glycerin, Aloe Barbadensis Bisabolol , PEG-8, Disodium EDTA, Polysorbate-20, PEG-40, Sorbitan Peroleate, Allantoin, Sodium Benzoate, Fragrance

Questions?

(800) 638-8149

PRINCIPAL DISPLAY PANEL - 281 ml Bottle Label

Makéta™

antimicrobial
FOAMING HAND
SANITIZER

kills 99.99%
of all germs

9.5 fl. oz. (281 ml)